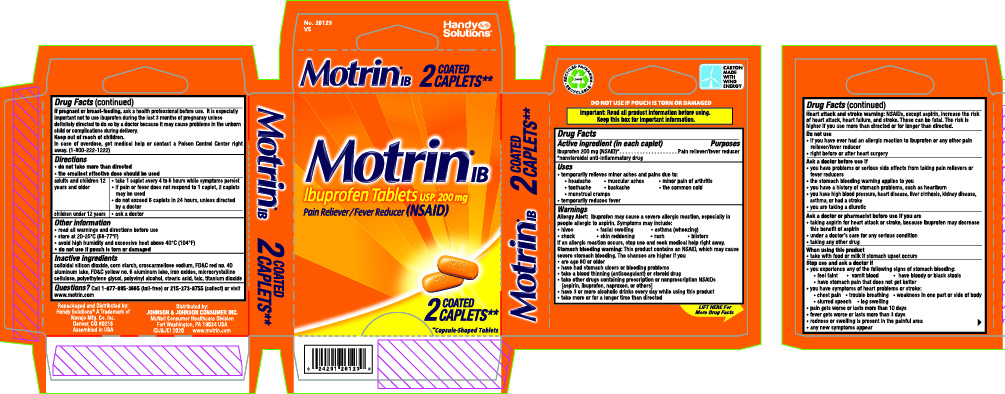 DRUG LABEL: Motrin IB
NDC: 67751-120 | Form: TABLET, FILM COATED
Manufacturer: Navajo Manufacturing Company Inc.
Category: otc | Type: HUMAN OTC DRUG LABEL
Date: 20230316

ACTIVE INGREDIENTS: IBUPROFEN 200 mg/1 1
INACTIVE INGREDIENTS: CARNAUBA WAX; SILICON DIOXIDE; STARCH, CORN; FD&C YELLOW NO. 6; HYPROMELLOSE, UNSPECIFIED; FERRIC OXIDE RED; MAGNESIUM STEARATE; POLYDEXTROSE; POLYETHYLENE GLYCOL, UNSPECIFIED; PROPYLENE GLYCOL; SHELLAC; STEARIC ACID; TITANIUM DIOXIDE

Motrin IB

Active ingredient (in each caplet)

Ibuprofen 200 mg (NSAID)*

*nonsteroidal anti-inflammatory drug

Purpose

Pain reliever/fever reducer

Uses

• temporarily relieves minor aches and pains due to:
• headache • muscular aches • minor pain of arthritis
• toothache • backache • the common cold
• menstrual cramps
• temporarily reduces fever

Warnings

Allergy Alert: Ibuprofen may cause a severe allergic reaction, especially in people allergic to aspirin. Symptoms may include:
• hives • facial swelling • asthma (wheezing)
• shock • skin reddening • rash • blisters
If an allergic reaction occurs, stop use and seek medical help right away.

Stomach bleeding warning: This product contains an NSAID, which may cause severe stomach bleeding. The chance is higher if you:
• are age 60 or older
• have had stomach ulcers or bleeding problems
• take a blood thinning (anticoagulant) or steroid drug
• take other drugs containing prescription or nonprescription NSAIDs (aspirin, ibuprofen, naproxen, or others)
• have 3 or more alcoholic drinks every day while using this product
• take more or for a longer time than directed

Heart attack and stroke warning: NSAIDs, except aspirin, increase the risk of heart attack, heart failure, and stroke. These can be fatal. The risk is higher if you use more than directed or for longer than directed.

Do not use

• if you have ever had an allergic reaction to any other pain reliever/fever reducer
• right before or after heart surgery

Ask a doctor before use if

• you have problems or serious side effects from taking pain relievers or fever reducers
• the stomach bleeding warning applies to you
• you have a history of stomach problems, such as heartburn
• you have high blood pressure, heart disease, liver cirrhosis, kidney disease, asthma, or had a stroke
• you are taking a diuretic

Ask a doctor or pharmacist before use if you are

• taking aspirin for heart attack or stroke, because ibuprofen may decrease this benefit of aspirin
• under a doctor’s care for any serious condition
• taking any other drug

When using this product

• take with food or milk if stomach upset occurs

Stop use and ask a doctor if

• you experience any of the following signs of stomach bleeding:
• feel faint • vomit blood • have bloody or black stools • have stomach pain that does not get better

• you have symptoms of heart problems or stroke:

• chest pain • trouble breathing • weakness in one part or side of body • slurred speech • leg swelling

• pain gets worse or lasts more than 10 days
• fever gets worse or lasts more than 3 days
• redness or swelling is present in the painful area
• any new symptoms appear

If pregnant or breast-feeding,

ask a health professional before use. It is especially important not to use ibuprofen during the last 3 months of pregnancy unless definitely directed to do so by a doctor because it may cause problems in the unborn child or complications during delivery.

Keep out of reach of children.

In case of overdose, get medical help or contact a Poison Control Center right away. (1-800-222-1222).

Directions

do not take more than directed
the smallest effective dose should be used

adults and children 12 years and older | • take 1 caplet every 4 to 6 hours while symptoms persist; • if pain or fever does not respond to 1 caplet, 2 caplets may be used; • do not exceed 6 caplets in 24 hours, unless directed by a doctor
children under 12 years | • ask a doctor

Other information

• read all warnings and directions before use

• store at 20-25ºC (68-77ºF)

• avoid high humidity and excessive heat above 40°C (104°F)

• do not use if pouch is torn or damaged

Inactive ingredients

colloidal silicon dioxide, corn starch, croscarmellose sodium, FD&C red no. 40 aluminum lake, FD&C yellow no. 6 aluminum lake, iron oxides, microcrystalline cellulose, polyethylene glycol, polyvinyl alcohol, stearic acid, talc, titanium dioxide

Questions or Comments?

Call 1-877-895-3665 (toll-free) or 215-273-8755 (collect) or visit www.motrin.com